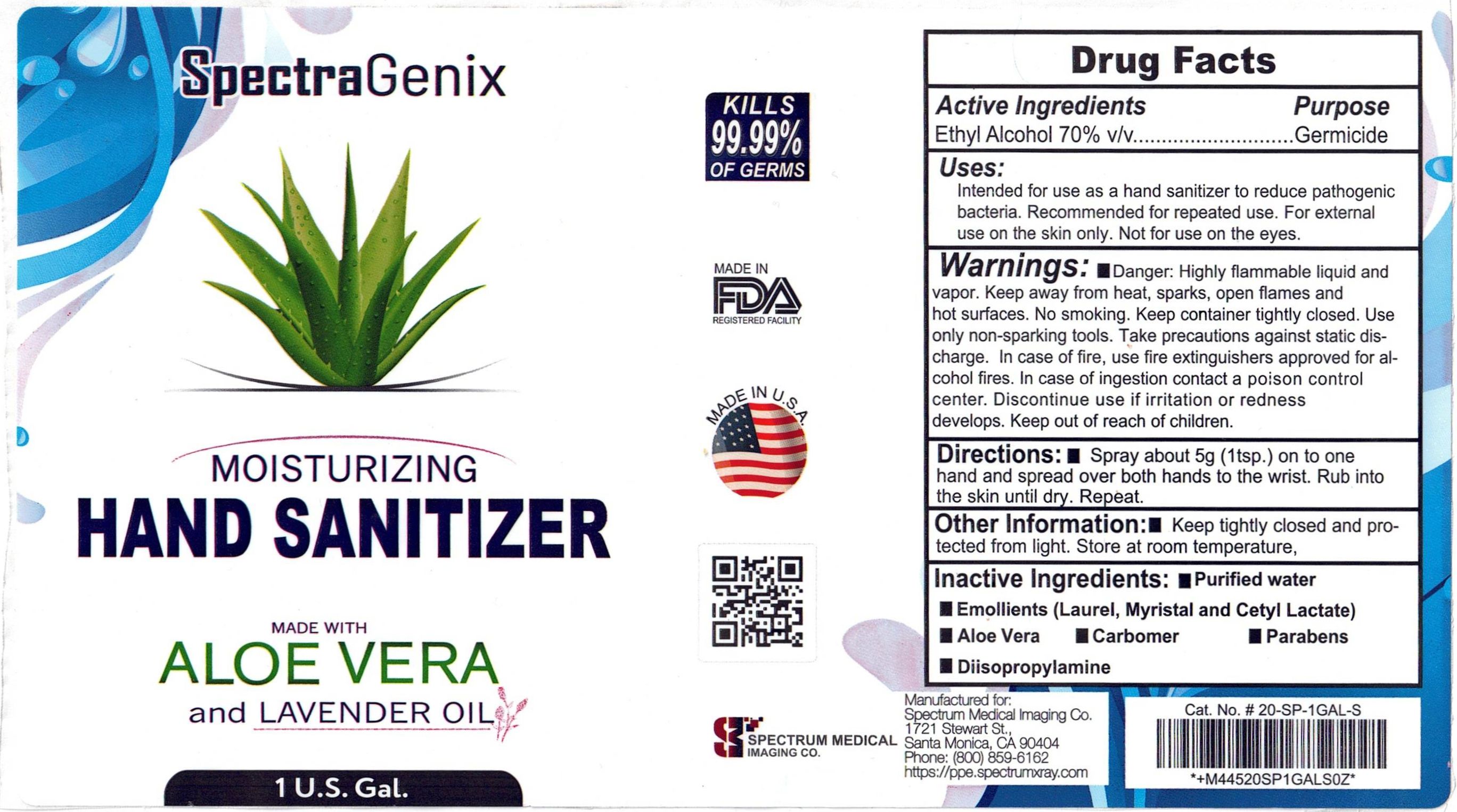 DRUG LABEL: SpectraGenix Hand Sanitizer
NDC: 12745-851 | Form: LIQUID
Manufacturer: Medical Chemical Corporation
Category: otc | Type: HUMAN OTC DRUG LABEL
Date: 20220117

ACTIVE INGREDIENTS: ALCOHOL 55.34 g/100 mL
INACTIVE INGREDIENTS: SPIKE LAVENDER OIL 0.02 g/100 mL; CARBOMER HOMOPOLYMER TYPE C 4 g/100 mL; CETYL LACTATE 0.5 g/100 mL; ALOE VERA LEAF 0.5 g/100 mL; DIISOPROPYLAMINE 0.29 g/100 mL; WATER

SpectraGenix Hand Sanitizer

Purpose

Germicide

Active Ingredients

Ethyl Alcohol 70% v/v

Inactive Ingredients

Purified water, Emollients (Laurel, Myristal and Cetyl Lactate,), Aloe Vera, Carbomer, Parabens, Diisopropylamine

Warnings

Warnings: Flammable, keep away from fire or flame. For external use only. Do no use in the eyes. Discontinue use if irritation or redness develops. Keep out of reach of children. In case of ingestion contact poison control center immediately.

Warnings

Danger: Highly flammable liqid and vapor. Keep away from heat, sparks, open flames and hot surfaces. No smoking. Keep container tightly closed. Use only non-sparking tools. Take precautions against static discharge. In case of fire, use fire extinguishers approved for alcohol fires. In case of ingestion contact a poison control center. Discontinue use if irritation or redness develops. Keep out of reach of children.

Directions

Spray about 5 g (1 tsp.) on to one hand and spread over both hands to the wrist. Rub into the skin until dry. Repeat.

Uses

Intended for use as a hand sanitizer to reduce pathogenic bacteria. Recommended for repeated use. For external use on the skin only. Not for use on the eyes.

PACKAGE LABEL

spectragenixlabel.jpg